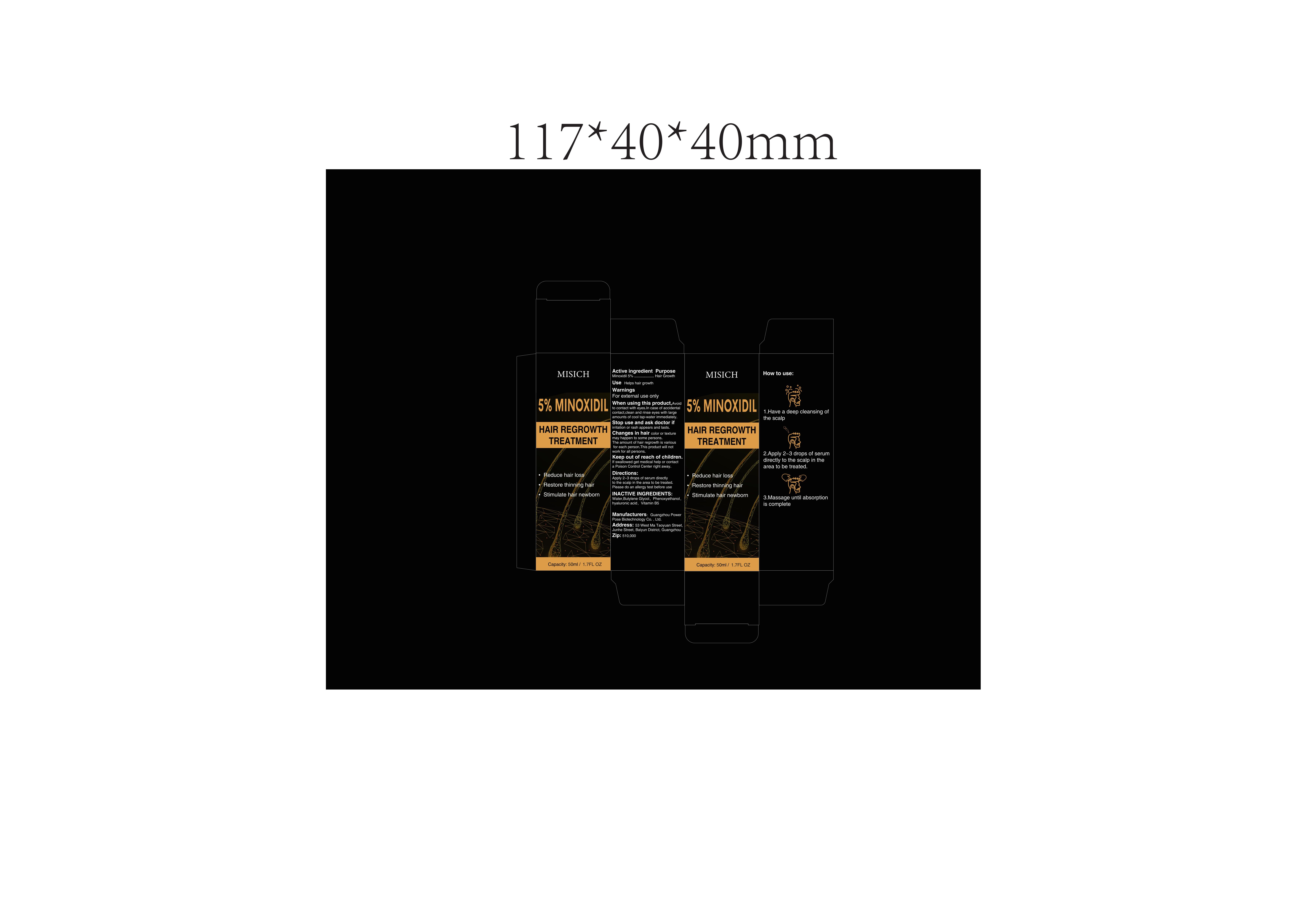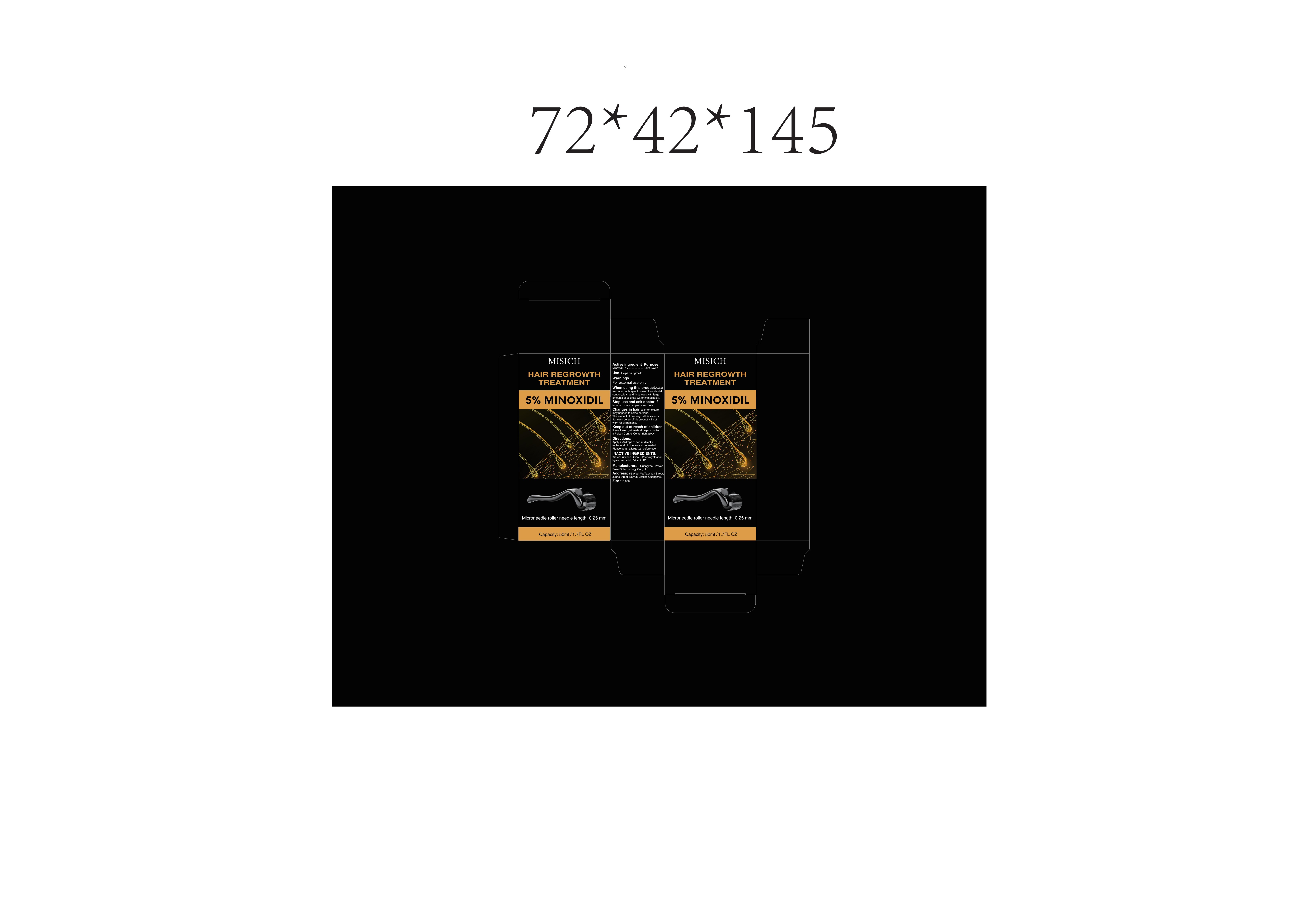 DRUG LABEL: Misich HAIR REGROWTH TREATMENT
NDC: 84213-002 | Form: LIQUID
Manufacturer: Shenzhen Weilaiwang Technology Co., Ltd
Category: otc | Type: HUMAN OTC DRUG LABEL
Date: 20240407

ACTIVE INGREDIENTS: MINOXIDIL 5 g/100 mL
INACTIVE INGREDIENTS: PHENOXYETHANOL; HYALURONIC ACID; PANTOTHENIC ACID; WATER; BUTYLENE GLYCOL

84213-002

Active Ingredient

Minoxidil 5%

Purpose

Hair Growth

Use

Helps hair growth

Warnings

For external use only

Do not use on injured skin

When Using

Avoid to contact with eyes.In case of accidental contact,clean and rinse eyes with large amounts of cool tap-water immediately.

Stop Use

irritation or rash appears and lasts.

Ask Doctor

irritation or rash appears and lasts.

Keep Oot Of Reach Of Children

If swallowed get medical help or contact a Poison Control Center right away.

Directions

Apply 2~3 drops of serum directly to the scalp in the area to be treated.
Please do an allergy test before use

Other information

Please do an allergy test before use

Inactive ingredients

Water，Minoxidil,Butylene Glycol，Phenoxyethanol，hyaluronic acid，Vitamin B5